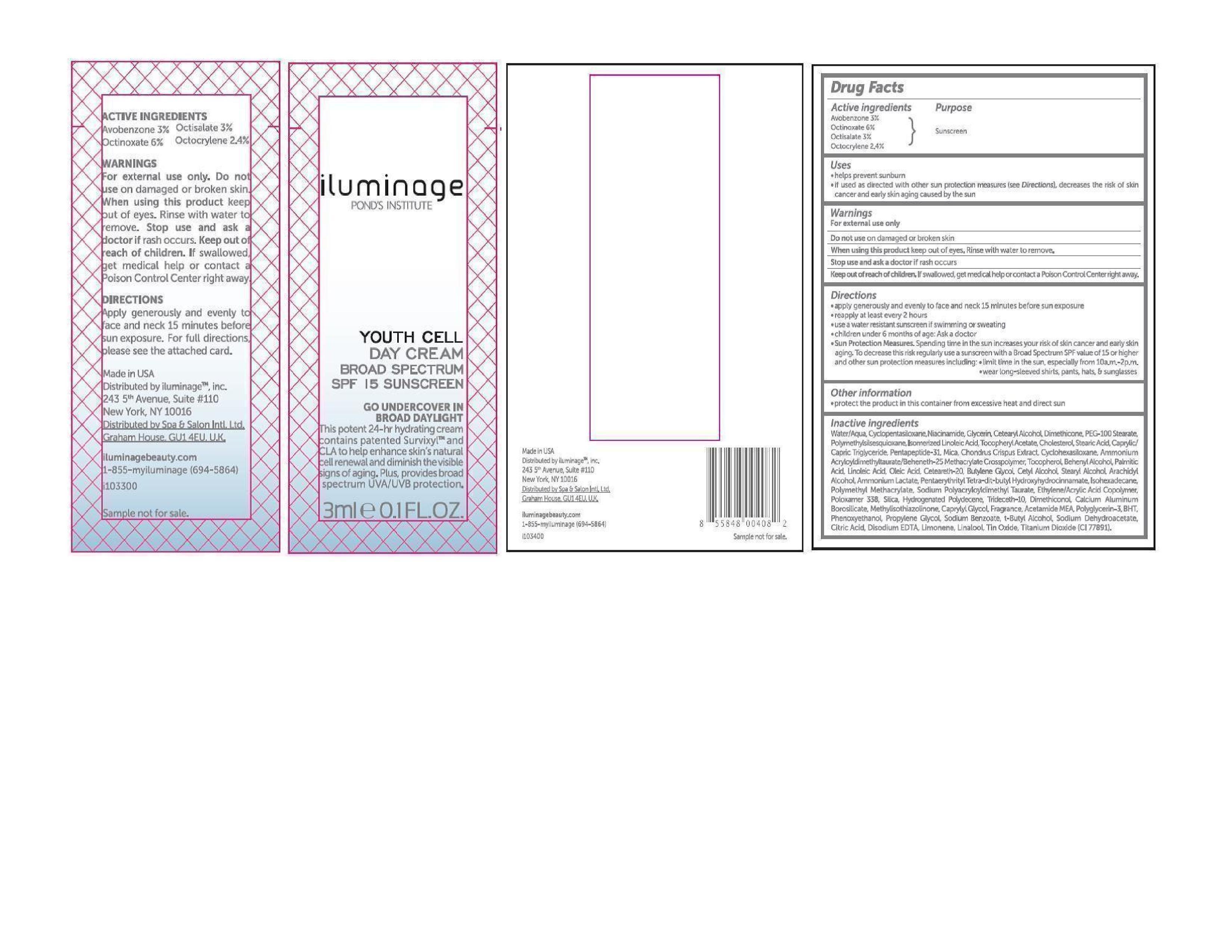 DRUG LABEL: Youth Cell Day
NDC: 69047-001 | Form: CREAM
Manufacturer: Iluminage Beauty, Inc.
Category: otc | Type: HUMAN OTC DRUG LABEL
Date: 20150107

ACTIVE INGREDIENTS: OCTINOXATE 6 mg/100 mL; OCTISALATE 3 mg/100 mL; OCTOCRYLENE 2.4 mg/100 mL; AVOBENZONE 3 mg/100 mL
INACTIVE INGREDIENTS: ACETAMIDE; AMMONIUM ACRYLOYLDIMETHYLTAURATE/BEHENETH-25 METHACRYLATE CROSSPOLYMER (52000 MPA.S); AMMONIUM LACTATE; ARACHIDYL ALCOHOL; DOCOSANOL; BUTYLATED HYDROXYTOLUENE; BUTYLENE GLYCOL; CALCIUM ALUMINUM BOROSILICATE; MEDIUM-CHAIN TRIGLYCERIDES; CAPRYLYL GLYCOL; POLYOXYL 20 CETOSTEARYL ETHER; CETOSTEARYL ALCOHOL; CETYL ALCOHOL; CHLORPHENESIN; CHOLESTEROL; CHONDRUS CRISPUS; CITRIC ACID MONOHYDRATE; CYCLOMETHICONE 6; CYCLOMETHICONE 5; CYCLOMETHICONE 4; DIMETHICONE; DIMETHICONOL (2000 CST); EDETATE DISODIUM; GLYCERIN; HYDROGENATED POLYDECENE (550 MW); ISOHEXADECANE; LINOLEIC ACID; METHYLISOTHIAZOLINONE; MICA; NIACINAMIDE; OLEIC ACID; PALMITIC ACID; PEG-100 STEARATE; PENTAERYTHRITOL TETRAKIS(3-(3,5-DI-TERT-BUTYL-4-HYDROXYPHENYL)PROPIONATE); PHENOXYETHANOL; POLOXAMER 338; POLY(METHYL METHACRYLATE; 450000 MW); POLYMETHYLSILSESQUIOXANE (4.5 MICRONS); PROPYLENE GLYCOL; SILICON DIOXIDE; SODIUM BENZOATE; SODIUM DEHYDROACETATE; STEARIC ACID; STEARYL ALCOHOL; TERT-BUTYL ALCOHOL; STANNIC OXIDE; TITANIUM DIOXIDE; .ALPHA.-TOCOPHEROL ACETATE; TRIDECETH-10; WATER

Drug Facts

Active Ingredients

Avobenzone 3%

Octinoxate 6%

Octisalate 3%

Octocrylene 2.4%

Purpose

Sunscreen

Uses

helps prevent sunburn

if used as directed with other sun protection measures (see Directions), decreases the risk of skin cancer and early skin aging caused by the sun

Warnings

For external use only

Do not use on damaged or broken skin

When using this product keep out of eyes. Rinse with water to remove.

Stop use and ask a doctor if rash occurs

Keep out of reach of children. If swallowed, get medical help or contact a Poison Control Center right away.

Directions

- apply liberally 15 minutes before sun exposure
- reapply at least every two hours
- use a water resistant sunscreen if swimming or sweating
- children under 6 months of age: ask a doctor
- Sun Protection Measures. Spending time in the sun increases your risk of skin cancer and early skin aging. To decrease this risk, regularly use a sunscreen with a Broad Spectrum SPF value of 15 or higher and other sun protection measures including:

- limit time in the sun, especially from 10 a.m.–2 p.m.

- wear long-sleeved shirts, pants, hats and sunglasses

Inactive ingredients

Water/Aqua, Cyclopentasiloxane, Nia-

cinamide, Glycerin, Cetearyl Alcohol,

Dimethicone, PEG-100 Stearate, Poly-

Methylsilsesquixane, Isomerized Linoleic

Acid, Tocopheryl Acetate, Cholesterol,

Stearic Acid, Caprylic/Capric Triglyceride,

Pentapeptide-31, Ammonium

Acryloydimethyltaurate/Beheneth-25

Methylacrylate Crosspolymer, Tocopherol,

Behenyl Alcoho, Palmitic Acid, Linoleic

Acid, Oleic Acid, Ceteareth-20, Butylene

Glycol, Cetyl Alcohol, Stearyl Alcohol,

Arachidyl Alcohol, Ammonium Lactate,

Pentaerythiryl Tetra-di-t-butyl Hydro-

Xyhydrocinnamate, Isohexadecane, Poly-

Methyl Methacrylate, Sodium Polyacry-

Loyldimethyl Taurate, Ethylene/Arcylic

Acid Copolymer, Poloxamer 338, Silica,

Hydrogenated Polydecene, Trideceth-10,

Dimethiconol, Calcium Aluminum

Borosilicate, Methylisothiszolinone, Cap-

prylyl Glycol, Fragrance, Acetamide MEA,

Polyglycerin-3, BHT, Phenoxyethanol,

Propylene Glycol, Sodium Benzoate,

Citric Acid, Disodium EDTA, Limonene,

Linalool, tin Oxide. Titanium Dioxide

(CI 77891).

Other information

protect the product in this container from excessive heat and direct sun

Label